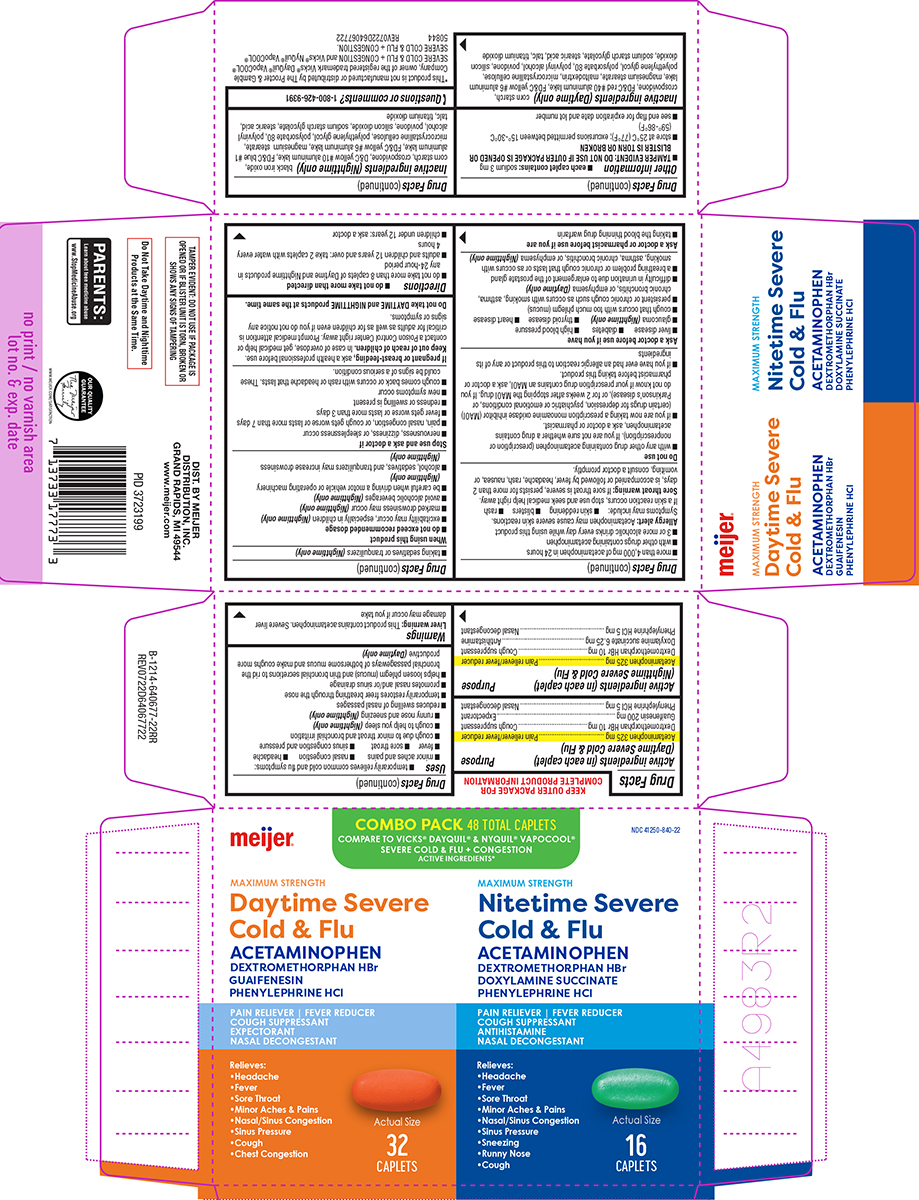 DRUG LABEL: DayTime/NiteTime Severe Cold and Flu
NDC: 41250-840 | Form: KIT | Route: ORAL
Manufacturer: Meijer Distribution Inc
Category: otc | Type: HUMAN OTC DRUG LABEL
Date: 20260209

ACTIVE INGREDIENTS: ACETAMINOPHEN 325 mg/1 1; DEXTROMETHORPHAN HYDROBROMIDE 10 mg/1 1; GUAIFENESIN 200 mg/1 1; PHENYLEPHRINE HYDROCHLORIDE 5 mg/1 1; ACETAMINOPHEN 325 mg/1 1; DEXTROMETHORPHAN HYDROBROMIDE 10 mg/1 1; DOXYLAMINE SUCCINATE 6.25 mg/1 1; PHENYLEPHRINE HYDROCHLORIDE 5 mg/1 1
INACTIVE INGREDIENTS: STARCH, CORN; CROSPOVIDONE, UNSPECIFIED; FD&C RED NO. 40 ALUMINUM LAKE; FD&C YELLOW NO. 6 ALUMINUM LAKE; MAGNESIUM STEARATE; MALTODEXTRIN; MICROCRYSTALLINE CELLULOSE; POLYETHYLENE GLYCOL, UNSPECIFIED; POLYSORBATE 80; POLYVINYL ALCOHOL, UNSPECIFIED; POVIDONE, UNSPECIFIED; SILICON DIOXIDE; SODIUM STARCH GLYCOLATE TYPE A POTATO; STEARIC ACID; TALC; TITANIUM DIOXIDE; FERROSOFERRIC OXIDE; STARCH, CORN; CROSPOVIDONE, UNSPECIFIED; D&C YELLOW NO. 10 ALUMINUM LAKE; FD&C BLUE NO. 1 ALUMINUM LAKE; FD&C YELLOW NO. 6 ALUMINUM LAKE; MAGNESIUM STEARATE; MICROCRYSTALLINE CELLULOSE; POLYETHYLENE GLYCOL, UNSPECIFIED; POLYSORBATE 80; POLYVINYL ALCOHOL, UNSPECIFIED; POVIDONE, UNSPECIFIED; SILICON DIOXIDE; SODIUM STARCH GLYCOLATE TYPE A POTATO; STEARIC ACID; TALC; TITANIUM DIOXIDE

Meijer 44-640677-22

Active ingredients (in each caplet) (Daytime Severe Cold & Flu)

Acetaminophen 325 mg
Dextromethorphan HBr 10 mg
Guaifenesin 200 mg
Phenylephrine HCl 5 mg

Purpose

Pain reliever/fever reducer
Cough suppressant
Expectorant
Nasal decongestant

Active ingredients (in each caplet) (Nighttime Severe Cold & Flu)

Acetaminophen 325 mg
Dextromethorphan HBr 10 mg
Doxylamine succinate 6.25 mg
Phenylephrine HCl 5 mg

Purpose

Pain reliever/fever reducer
Cough suppressant
Antihistamine
Nasal decongestant

Uses

- temporarily relieves common cold and flu symptoms:
  - minor aches and pains
  - nasal congestion
  - headache
  - fever
  - sore throat
  - sinus congestion and pressure
  - cough due to minor throat and bronchial irritation
  - cough to help you sleep (Nighttime only)
  - runny nose and sneezing (Nighttime only)
- reduces swelling of nasal passages
- temporarily restores freer breathing through the nose
- promotes nasal and/or sinus drainage
- helps loosen phlegm (mucus) and thin bronchial secretions to rid the bronchial passageways of bothersome mucus and make coughs more productive (Daytime only)

Warnings

Liver warning: This product contains acetaminophen. Severe liver damage may occur if you take

- more than 4,000 mg of acetaminophen in 24 hours
- with other drugs containing acetaminophen
- 3 or more alcoholic drinks every day while using this product

Allergy alert: Acetaminophen may cause severe skin reactions. Symptoms may include:

- skin reddening
- blisters
- rash

If a skin reaction occurs, stop use and seek medical help right away.

Sore throat warning: If sore throat is severe, persists for more than 2 days, is accompanied or followed by fever, headache, rash, nausea, or vomiting, consult a doctor promptly.

Do not use

- with any other drug containing acetaminophen (prescription or nonprescription). If you are not sure whether a drug contains acetaminophen, ask a doctor or pharmacist.
- if you are now taking a prescription monoamine oxidase inhibitor (MAOI) (certain drugs for depression, psychiatric or emotional conditions, or Parkinson’s disease), or for 2 weeks after stopping the MAOI drug. If you do not know if your prescription drug contains an MAOI, ask a doctor or pharmacist before taking this product.
- if you have ever had an allergic reaction to this product or any of its ingredients

Ask a doctor before use if you have

- liver disease
- diabetes
- high blood pressure
- glaucoma (Nighttime only)
- thyroid disease
- heart disease
- cough that occurs with too much phlegm (mucus)
- persistent or chronic cough such as occurs with smoking, asthma, chronic bronchitis, or emphysema (Daytime only)
- difficulty in urination due to enlargement of the prostate gland
- a breathing problem or chronic cough that lasts or as occurs with smoking, asthma, chronic bronchitis, or emphysema (Nighttime only)

Ask a doctor or pharmacist before use if you are

- taking the blood thinning drug warfarin
- taking sedatives or tranquilizers (Nighttime only)

When using this product

- do not exceed recommended dosage
- excitability may occur, especially in children (Nighttime only)
- marked drowsiness may occur (Nighttime only)
- avoid alcoholic beverages (Nighttime only)
- be careful when driving a motor vehicle or operating machinery (Nighttime only)
- alcohol, sedatives, and tranquilizers may increase drowsiness (Nighttime only)

Stop use and ask a doctor if

- nervousness, dizziness, or sleeplessness occur
- pain, nasal congestion, or cough gets worse or lasts more than 7 days
- fever gets worse or lasts more than 3 days
- redness or swelling is present
- new symptoms occur
- cough comes back or occurs with rash or headache that lasts. These could be signs of a serious condition.

If pregnant or breast-feeding,

ask a health professional before use.

Keep out of reach of children.

In case of overdose, get medical help or contact a Poison Control Center right away. Prompt medical attention is critical for adults as well as for children even if you do not notice any signs or symptoms.

Do not take DAYTIME and NIGHTTIME products at the same time.

Directions

- do not take more than directed
- do not take more than 8 caplets of Daytime and Nighttime products in any 24-hour period
- adults and children 12 years and over: take 2 caplets with water every 4 hours
- children under 12 years: ask a doctor

Other information

- each caplet contains: sodium 3 mg
- TAMPER EVIDENT: DO NOT USE IF OUTER PACKAGE IS OPENED OR BLISTER IS TORN OR BROKEN
- store at 25°C (77°F); excursions permitted between 15°-30°C (59°-86°F)
- see end flap for expiration date and lot number

Inactive ingredients (Daytime only)

corn starch, crospovidone, FD&C red #40 aluminum lake, FD&C yellow #6 aluminum lake, magnesium stearate, maltodextrin, microcrystalline cellulose, polyethylene glycol, polysorbate 80, polyvinyl alcohol, povidone, silicon dioxide, sodium starch glycolate, stearic acid, talc, titanium dioxide

Inactive ingredients (Nighttime only)

black iron oxide, corn starch, crospovidone, D&C yellow #10 aluminum lake, FD&C blue #1 aluminum lake, FD&C yellow #6 aluminum lake, magnesium stearate, microcrystalline cellulose, polyethylene glycol, polysorbate 80, polyvinyl alcohol, povidone, silicon dioxide, sodium starch glycolate, stearic acid, talc, titanium dioxide

Questions or comments?

1-800-426-9391

Principal Display Panel

meijer®

COMBO PACK 48 TOTAL CAPLETS
COMPARE TO VICKS® DAYQUIL® & NYQUIL® VAPOCOOL®
SEVERE COLD & FLU + CONGESTION
ACTIVE INGREDIENTS*
NDC 41250-840-22

MAXIMUM STRENGTH
Daytime Severe
Cold & Flu
ACETAMINOPHEN
DEXTROMETHORPHAN HBr
GUAIFENESIN
PHENYLEPHRINE HCl
PAIN RELIEVER | FEVER REDUCER
COUGH SUPPRESSANT
EXPECTORANT
NASAL DECONGESTANT
Relieves:
•Headache
•Fever
•Sore Throat
•Minor Aches & Pains
•Nasal/Sinus Congestion
•Sinus Pressure
•Cough
•Chest Congestion
32
Caplets
Actual Size

MAXIMUM STRENGTH
Nitetime Severe
Cold & Flu

ACETAMINOPHEN
DEXTROMETHORPHAN HBr
DOXYLAMINE SUCCINATE
PHENYLEPHRINE HCl
PAIN RELIEVER | FEVER REDUCER
COUGH SUPPRESSANT
ANTIHISTAMINE
NASAL DECONGESTANT
Relieves:
•Headache
•Fever
•Sore Throat
•Minor Aches & Pains
•Nasal/Sinus Congestion
•Sinus Pressure
•Sneezing
•Runny Nose
•Cough
16
Caplets
Actual Size

TAMPER EVIDENT: DO NOT USE IF PACKAGE IS
OPENED OR IF BLISTER UNIT IS TORN, BROKEN
OR SHOWS ANY SIGNS OF TAMPERING

PARENTS:
Learn about teen medicine abuse
www.StopMedicineAbuse.org

Do Not Take Daytime and Nighttime
Products at the Same Time.

*This product is not manufactured or distributed by The Procter & Gamble
Company, owner of the registered trademark Vicks® DayQuil® VapoCOOL®
SEVERE COLD & FLU + CONGESTION and Vicks® NyQuil® VapoCOOL®
SEVERE COLD & FLU + CONGESTION.
50844 REV0722D64067722

DIST. BY MEIJER
DISTRIBUTION, INC.
GRAND RAPIDS, MI 49544
www.meijer.com

Meijer 44-640677